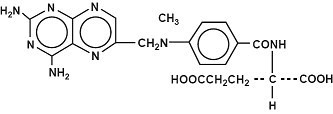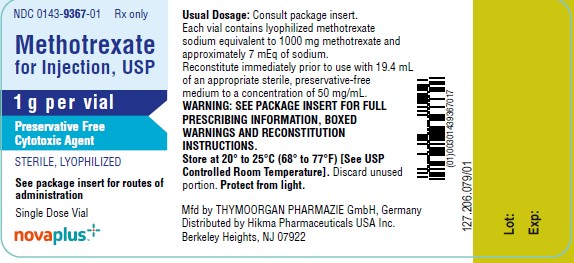 DRUG LABEL: Methotrexate
NDC: 0143-9367 | Form: INJECTION, POWDER, LYOPHILIZED, FOR SOLUTION
Manufacturer: Hikma Pharmaceuticals USA Inc.
Category: prescription | Type: HUMAN PRESCRIPTION DRUG LABEL
Date: 20240905

ACTIVE INGREDIENTS: METHOTREXATE 1 g/1 1
INACTIVE INGREDIENTS: HYDROCHLORIC ACID; SODIUM HYDROXIDE

METHOTREXATE INJECTION, USP
METHOTREXATE FOR INJECTION, USP

Rx only

WARNINGS

- FOR INTRATHECAL AND HIGH-DOSE THERAPY, USE THE PRESERVATIVE-FREE FORMULATION OF METHOTREXATE. DO NOT USE THE PRESERVED FORMULATION FOR INTRATHECAL OR HIGH-DOSE THERAPY BECAUSE IT CONTAINS BENZYL ALCOHOL.
- METHOTREXATE SHOULD BE USED ONLY IN LIFE THREATENING NEOPLASTIC DISEASES, OR IN PATIENTS WITH PSORIASIS OR RHEUMATOID ARTHRITIS WITH SEVERE, RECALCITRANT, DISABLING DISEASE WHICH IS NOT ADEQUATELY RESPONSIVE TO OTHER FORMS OF THERAPY.
- DEATHS HAVE BEEN REPORTED WITH THE USE OF METHOTREXATE IN THE TREATMENT OF MALIGNANCY, PSORIASIS, AND RHEUMATOID ARTHRITIS.
- PATIENTS SHOULD BE CLOSELY MONITORED FOR BONE MARROW, LIVER, LUNG AND KIDNEY TOXICITIES. (See PRECAUTIONS.)
- PATIENTS SHOULD BE INFORMED BY THEIR PHYSICIAN OF THE RISKS INVOLVED AND BE UNDER A PHYSICIAN’S CARE THROUGHOUT THERAPY.
- THE USE OF METHOTREXATE HIGH-DOSE REGIMENS RECOMMENDED FOR OSTEOSARCOMA REQUIRES METICULOUS CARE. (See DOSAGE AND ADMINISTRATION.) HIGH-DOSE REGIMENS FOR OTHER NEOPLASTIC DISEASES ARE INVESTIGATIONAL AND A THERAPEUTIC ADVANTAGE HAS NOT BEEN ESTABLISHED.
- Methotrexate has been reported to cause fetal death and/or congenital anomalies. Therefore, it is not recommended for women of childbearing potential unless there is clear medical evidence that the benefits can be expected to outweigh the considered risks. Pregnant women with psoriasis or rheumatoid arthritis should not receive methotrexate (See CONTRAINDICATIONS).
- Methotrexate elimination is reduced in patients with impaired renal functions, ascites, or pleural effusions. Such patients require especially careful monitoring for toxicity, and require dose reduction or, in some cases, discontinuation of methotrexate administration.
- Unexpectedly severe (sometimes fatal) bone marrow suppression, aplastic anemia, and gastrointestinal toxicity have been reported with concomitant administration of methotrexate (usually in high dosage) along with some nonsteroidal anti-inflammatory drugs (NSAIDs). (See PRECAUTIONS, Drug Interactions.)
- Methotrexate causes hepatotoxicity, fibrosis and cirrhosis, but generally only after prolonged use. Acutely, liver enzyme elevations are frequently seen. These are usually transient and asymptomatic, and also do not appear predictive of subsequent hepatic disease. Liver biopsy after sustained use often shows histologic changes, and fibrosis and cirrhosis have been reported; these latter lesions may not be preceded by symptoms or abnormal liver function tests in the psoriasis population. For this reason, periodic liver biopsies are usually recommended for psoriatic patients who are under long-term treatment. Persistent abnormalities in liver function tests may precede appearance of fibrosis or cirrhosis in the rheumatoid arthritis population. (See PRECAUTIONS, Organ System Toxicity, Hepatic.)
- Methotrexate-induced lung disease, including acute or chronic interstitial pneumonitis, is a potentially dangerous lesion, which may occur acutely at any time during therapy and has been reported at low doses. It is not always fully reversible and fatalities have been reported. Pulmonary symptoms (especially a dry, nonproductive cough) may require interruption of treatment and careful investigation.
- Diarrhea and ulcerative stomatitis require interruption of therapy: otherwise, hemorrhagic enteritis and death from intestinal perforation may occur.
- Malignant lymphomas, which may regress following withdrawal of methotrexate, may occur in patients receiving low-dose methotrexate and, thus, may not require cytotoxic treatment. Discontinue methotrexate first and, if the lymphoma does not regress, appropriate treatment should be instituted.
- Like other cytotoxic drugs, methotrexate may induce “tumor lysis syndrome” in patients with rapidly growing tumors. Appropriate supportive and pharmacologic measures may prevent or alleviate this complication.
- Severe, occasionally fatal, skin reactions have been reported following single or multiple doses of methotrexate. Reactions have occurred within days of oral, intramuscular, intravenous, or intrathecal methotrexate administration. Recovery has been reported with discontinuation of therapy. (See PRECAUTIONS, Organ System Toxicity, Skin.)
- Potentially fatal opportunistic infections, especially Pneumocystis carinii pneumonia, may occur with methotrexate therapy.
- Methotrexate given concomitantly with radiotherapy may increase the risk of soft tissue necrosis and osteonecrosis.

DESCRIPTION

Methotrexate is an antimetabolite used in the treatment of certain neoplastic diseases, severe psoriasis, and adult rheumatoid arthritis.

Chemically methotrexate is L-(+)-N-[p-[[(2,4-Diamino-6-pteridinyl)methyl]methylamino]-benzoyl]glutamic acid.

The structural formula is:

Structural Formula

C20H22N8O5 M.W.=454.44

Methotrexate for injection (Preservative Free) is sterile and non-pyrogenic and may be given by the intramuscular, intravenous, intra-arterial or intrathecal route. (See DOSAGE AND ADMINISTRATION.)

Methotrexate for Injection, USP, Lyophilized, Preservative Free, for single use only, is available in 1 gram vials.

Each 1 gram vial of lyophilized powder contains methotrexate sodium equivalent to 1 gram methotrexate. Contains no preservative. Sodium hydroxide and, if necessary, hydrochloric acid are added during manufacture to adjust the pH. The 1 gram vial contains approximately 7 mEq sodium.

CLINICAL PHARMACOLOGY

Methotrexate inhibits dihydrofolic acid reductase. Dihydrofolates must be reduced to tetrahydrofolates by this enzyme before they can be utilized as carriers of one- carbon groups in the synthesis of purine nucleotides and thymidylate. Therefore, methotrexate interferes with DNA synthesis, repair, and cellular replication. Actively proliferating tissues such as malignant cells, bone marrow, fetal cells, buccal and intestinal mucosa, and cells of the urinary bladder are in general more sensitive to this effect of methotrexate. When cellular proliferation in malignant tissues is greater than in most normal tissues, methotrexate may impair malignant growth without irreversible damage to normal tissues.

The mechanism of action in rheumatoid arthritis is unknown; it may affect immune function. Two reports describe in vitro methotrexate inhibition of DNA precursor uptake by stimulated mononuclear cells, and another describes in animal polyarthritis partial correction by methotrexate of spleen cell hyporesponsiveness and suppressed IL 2 production. Other laboratories, however, have been unable to demonstrate similar effects. Clarification of methotrexate’s effect on immune activity and its relation to rheumatoid immunopathogenesis await further studies.

In patients with rheumatoid arthritis, effects of methotrexate on articular swelling and tenderness can be seen as early as 3 to 6 weeks. Although methotrexate clearly ameliorates symptoms of inflammation (pain, swelling, stiffness), there is no evidence that it induces remission of rheumatoid arthritis nor has a beneficial effect been demonstrated on bone erosions and other radiologic changes which result in impaired joint use, functional disability, and deformity.

Most studies of methotrexate in patients with rheumatoid arthritis are relatively short term (3 to 6 months). Limited data from long-term studies indicate that an initial clinical improvement is maintained for at least two years with continued therapy.

In psoriasis, the rate of production of epithelial cells in the skin is greatly increased over normal skin. This differential in proliferation rates is the basis for the use of methotrexate to control the psoriatic process.

Methotrexate in high doses, followed by leucovorin rescue, is used as a part of the treatment of patients with non-metastatic osteosarcoma. The original rationale for high-dose methotrexate therapy was based on the concept of selective rescue of normal tissues by leucovorin. More recent evidence suggests that high-dose methotrexate may also overcome methotrexate resistance caused by impaired active transport, decreased affinity of dihydrofolic acid reductase for methotrexate, increased levels of dihydrofolic acid reductase resulting from gene amplification, or decreased polyglutamation of methotrexate. The actual mechanism of action is unknown.

In a 6-month double-blind, placebo-controlled trial of 127 pediatric patients with juvenile rheumatoid arthritis (JRA) (mean age, 10.1 years; age range, 2.5 to 18 years; mean duration of disease, 5.1 years) on background nonsteroidal anti-inflammatory drugs (NSAIDs) and/or prednisone, methotrexate given weekly at an oral dose of 10 mg/m^2 provided significant clinical improvement compared to placebo as measured by either the physician’s global assessment, or by a patient composite (25% reduction in the articular-severity score plus improvement in parent and physician global assessments of disease activity). Over two-thirds of the patients in this trial had polyarticular-course JRA, and the numerically greatest response was seen in this subgroup treated with 10 mg/m^2/wk methotrexate. The overwhelming majority of the remaining patients had systemic-course JRA. All patients were unresponsive to NSAIDs; approximately one-third were using low dose corticosteroids. Weekly methotrexate at a dose of 5 mg/m^2 was not significantly more effective than placebo in this trial.

Two Pediatric Oncology Group studies (one randomized and one non-randomized) demonstrated a significant improvement in relapse-free survival in patients with non-metastatic osteosarcoma, when high-dose methotrexate with leucovorin rescue was used in combination with other chemotherapeutic agents following surgical resection of the primary tumor. These studies were not designed to demonstrate the specific contribution of high-dose methotrexate/leucovorin rescue therapy to the efficacy of the combination. However, a contribution can be inferred from the reports of objective responses to this therapy in patients with metastatic osteosarcoma, and from reports of extensive tumor necrosis following preoperative administration of this therapy to patients with non-metastatic osteosarcoma.

Pharmacokinetics

Absorption

Oral absorption appears to be dose dependent. Peak plasma concentrations are reached within 0.75 to 6 hours following oral administration. At doses of 30 mg/m^2 or less, methotrexate is generally well absorbed with a mean bioavailability of about 60%. The absorption of doses greater than 80 mg/m^2 is significantly less, possibly due to a saturation effect.

In leukemic pediatric patients, oral absorption of methotrexate also appears to be dose dependent and has been reported to vary widely (23% to 95%). A twenty fold difference between highest and lowest peak levels (Cmax: 0.11 to 2.3 micromolar after a 20 mg/m^2 dose) has been reported. Significant interindividual variability has also been noted in time to peak concentration (Tmax: 0.67 to 4 hrs after a 15 mg/m^2 dose) and fraction of dose absorbed. The absorption of doses greater than 40 mg/m^2 has been reported to be significantly less than that of lower doses. Food has been shown to delay absorption and reduce peak concentration. Methotrexate is generally completely absorbed from parenteral routes of injection. After intramuscular injection, peak serum concentrations occur in 30 to 60 minutes. As in leukemic pediatric patients, a wide interindividual variability in the plasma concentrations of methotrexate has been reported in pediatric patients with JRA. Following oral administration of methotrexate in doses of 6.4 to 11.2 mg/m^2/week in pediatric patients with JRA, mean serum concentrations were 0.59 micromolar (range, 0.03 to 1.40) at 1 hour, 0.44 micromolar (range, 0.01 to 1.00) at 2 hours, and 0.29 micromolar (range, 0.06 to 0.58) at 3 hours. In pediatric patients receiving methotrexate for acute lymphocytic leukemia (6.3 to 30 mg/m^2), or for JRA (3.75 to 26.2 mg/m^2), the terminal half-life has been reported to range from 0.7 to 5.8 hours or 0.9 to 2.3 hours, respectively.

Distribution

-After intravenous administration, the initial volume of distribution is approximately 0.18 L/kg (18% of body weight) and steady-state volume of distribution is approximately 0.4 to 0.8 L/kg (40 to 80% of body weight). Methotrexate competes with reduced folates for active transport across cell membranes by means of a single carrier-mediated active transport process. At serum concentrations greater than 100 micromolar, passive diffusion becomes a major pathway by which effective intracellular concentrations can be achieved. Methotrexate in serum is approximately 50% protein bound. Laboratory studies demonstrate that it may be displaced from plasma albumin by various compounds including sulfonamides, salicylates, tetracyclines, chloramphenicol, and phenytoin.

Methotrexate does not penetrate the blood-cerebrospinal fluid barrier in therapeutic amounts when given orally or parenterally. High CSF concentrations of the drug may be attained by intrathecal administration.

In dogs, synovial fluid concentrations after oral dosing were higher in inflamed than uninflamed joints. Although salicylates did not interfere with this penetration, prior prednisone treatment reduced penetration into inflamed joints to the level of normal joints.

Metabolism

After absorption, methotrexate undergoes hepatic and intracellular metabolism to polyglutamated forms which can be converted back to methotrexate by hydrolase enzymes. These polyglutamates act as inhibitors of dihydrofolate reductase and thymidylate synthetase. Small amounts of methotrexate polyglutamates may remain in tissues for extended periods. The retention and prolonged drug action of these active metabolites vary among different cells, tissues and tumors. A small amount of metabolism to 7-hydroxymethotrexate may occur at doses commonly prescribed. Accumulation of this metabolite may become significant at the high doses used in osteogenic sarcoma. The aqueous solubility of 7-hydroxymethotrexate is 3 to 5 fold lower than the parent compound. Methotrexate is partially metabolized by intestinal flora after oral administration.

Half-Life

The terminal half-life reported for methotrexate is approximately three to ten hours for patients receiving treatment for psoriasis, or rheumatoid arthritis or low dose antineoplastic therapy (less than 30 mg/m^2). For patients receiving high doses of methotrexate, the terminal half-life is eight to 15 hours.

Excretion

Renal excretion is the primary route of elimination and is dependent upon dosage and route of administration. With IV administration, 80% to 90% of the administered dose is excreted unchanged in the urine within 24 hours. There is limited biliary excretion amounting to 10% or less of the administered dose. Enterohepatic recirculation of methotrexate has been proposed.

Renal excretion occurs by glomerular filtration and active tubular secretion. Nonlinear elimination due to saturation of renal tubular reabsorption has been observed in psoriatic patients at doses between 7.5 and 30 mg. Impaired renal function, as well as concurrent use of drugs such as weak organic acids that also undergo tubular secretion, can markedly increase methotrexate serum levels. Excellent correlation has been reported between methotrexate clearance and endogenous creatinine clearance.

Methotrexate clearance rates vary widely and are generally decreased at higher doses. Delayed drug clearance has been identified as one of the major factors responsible for methotrexate toxicity. It has been postulated that the toxicity of methotrexate for normal tissues is more dependent upon the duration of exposure to the drug rather than the peak level achieved. When a patient has delayed drug elimination due to compromised renal function, a third space effusion, or other causes, methotrexate serum concentrations may remain elevated for prolonged periods.

The potential for toxicity from high-dose regimens or delayed excretion is reduced by the administration of leucovorin calcium during the final phase of methotrexate plasma elimination.

Pharmacokinetic monitoring of methotrexate serum concentrations may help identify those patients at high risk for methotrexate toxicity and aid in proper adjustments of leucovorin dosing. Guidelines for monitoring serum methotrexate levels, and for adjustment of leucovorin dosing to reduce the risk of methotrexate toxicity, are provided below in DOSAGE AND ADMINISTRATION.

Methotrexate has been detected in human breast milk. The highest breast milk to plasma concentration ratio reached was 0.08:1.

INDICATIONS AND USAGE

Neoplastic Diseases

Methotrexate is indicated in the treatment of gestational choriocarcinoma, chorioadenoma destruens and hydatidiform mole.

In acute lymphocytic leukemia, methotrexate is indicated in the prophylaxis of meningeal leukemia and is used in maintenance therapy in combination with other chemotherapeutic agents. Methotrexate is also indicated in the treatment of meningeal leukemia.

Methotrexate is used alone or in combination with other anticancer agents in the treatment of breast cancer, epidermoid cancers of the head and neck, advanced mycosis fungoides (cutaneous T cell lymphoma), and lung cancer, particularly squamous cell and small cell types. Methotrexate is also used in combination with other chemotherapeutic agents in the treatment of advanced stage non-Hodgkin’s lymphomas.

Methotrexate in high doses followed by leucovorin rescue in combination with other chemotherapeutic agents is effective in prolonging relapse-free survival in patients with non-metastatic osteosarcoma who have undergone surgical resection or amputation for the primary tumor.

Psoriasis:

Methotrexate is indicated in the symptomatic control of severe, recalcitrant, disabling psoriasis that is not adequately responsive to other forms of therapy, but only when the diagnosis has been established, as by a biopsy and/or after dermatologic consultation. It is important to ensure that a psoriasis “flare” is not due to an undiagnosed concomitant disease affecting immune responses.

Rheumatoid Arthritis including Polyarticular-Course Juvenile Rheumatoid Arthritis:

Methotrexate is indicated in the management of selected adults with severe, active rheumatoid arthritis (ACR criteria), or children with active polyarticular-course juvenile rheumatoid arthritis, who have had an insufficient therapeutic response to, or are intolerant of, an adequate trial of first-line therapy including full dose non- steroidal anti-inflammatory agents (NSAIDs).

Aspirin, (NSAIDs), and/or low dose steroids may be continued, although the possibility of increased toxicity with concomitant use of NSAIDs including salicylates has not been fully explored. (See PRECAUTIONS, Drug Interactions.) Steroids may be reduced gradually in patients who respond to methotrexate. Combined use of methotrexate with gold, penicillamine, hydroxychloroquine, sulfasalazine, or cytotoxic agents, has not been studied and may increase the incidence of adverse effects. Rest and physiotherapy as indicated should be continued.

CONTRAINDICATIONS

Methotrexate can cause fetal death or teratogenic effects when administered to a pregnant woman. Methotrexate is contraindicated in pregnant women with psoriasis or rheumatoid arthritis and should be used in the treatment of neoplastic diseases only when the potential benefit outweighs the risk to the fetus. Women of childbearing potential should not be started on methotrexate until pregnancy is excluded and should be fully counseled on the serious risk to the fetus (see PRECAUTIONS) should they become pregnant while undergoing treatment. Pregnancy should be avoided if either partner is receiving methotrexate; during and for a minimum of three months after therapy for male patients, and during and for at least one ovulatory cycle after therapy for female patients. (see Boxed WARNINGS).

Because of the potential for serious adverse reactions from methotrexate in breast fed infants, it is contraindicated in nursing mothers.

Patients with psoriasis or rheumatoid arthritis with alcoholism, alcoholic liver disease or other chronic liver disease should not receive methotrexate.

Patients with psoriasis or rheumatoid arthritis who have overt or laboratory evidence of immunodeficiency syndromes should not receive methotrexate.

Patients with psoriasis or rheumatoid arthritis who have preexisting blood dyscrasias, such as bone marrow hypoplasia, leukopenia, thrombocytopenia, or significant anemia, should not receive methotrexate.

Patients with a known hypersensitivity to methotrexate should not receive the drug.

WARNINGS

WARNINGS – SEE BOXED WARNINGS.

For intrathecal and high-dose methotrexate therapy, use the preservative-free formulation of methotrexate. Do not use the preserved formulation of methotrexate for intrathecal or high-dose therapy because it contains benzyl alcohol.

Use caution when administering high-dose methotrexate to patients receiving proton pump inhibitor (PPI) therapy. Case reports and published population pharmacokinetic studies suggest that concomitant use of some PPIs, such as omeprazole, esomeprazole, and pantoprazole, with methotrexate (primarily at high doses), may elevate and prolong serum levels of methotrexate and/or its metabolite hydroxymethotrexate, possibly leading to methotrexate toxicities. In two of these cases, delayed methotrexate elimination was observed when high-dose methotrexate was co-administered with PPIs, but was not observed when methotrexate was co- administered with ranitidine. However, no formal drug interaction studies of methotrexate with ranitidine have been conducted.

PRECAUTIONS

General

Methotrexate has the potential for serious toxicity (see Boxed WARNINGS). Toxic effects may be related in frequency and severity to dose or frequency of administration but have been seen at all doses. Because they can occur at any time during therapy, it is necessary to follow patients on methotrexate closely. Most adverse reactions are reversible if detected early. When such reactions do occur, the drug should be reduced in dosage or discontinued and appropriate corrective measures should be taken. If necessary, this could include the use of leucovorin calcium and/or acute, intermittent hemodialysis with a high-flux dialyzer. (See OVERDOSAGE). If methotrexate therapy is reinstituted, it should be carried out with caution, with adequate consideration of further need for the drug and increased alertness as to possible recurrence of toxicity.

The clinical pharmacology of methotrexate has not been well studied in older individuals. Due to diminished hepatic and renal function as well as decreased folate stores in this population, relatively low doses should be considered, and these patients should be closely monitored for early signs of toxicity.

Some of the effects mentioned under ADVERSE REACTIONS, such as dizziness and fatigue, may affect the ability to drive or operate machinery.

Information for Patients

Patients should be informed of the early signs and symptoms of toxicity, of the need to see their physician promptly if they occur, and the need for close follow-up, including periodic laboratory tests to monitor toxicity.

Both the physician and pharmacist should emphasize to the patient that the recommended dose is taken weekly in rheumatoid arthritis and psoriasis, and that mistaken daily use of the recommended dose has led to fatal toxicity. Prescriptions should not be written or refilled on a PRN basis.

Patients should be informed of the potential benefit and risk in the use of methotrexate. The risk of effects on reproduction should be discussed with both male and female patients taking methotrexate.

Laboratory Tests

Patients undergoing methotrexate therapy should be closely monitored so that toxic effects are detected promptly. Baseline assessment should include a complete blood count with differential and platelet counts, hepatic enzymes, renal function tests and a chest X-ray. During therapy of rheumatoid arthritis and psoriasis, monitoring of these parameters is recommended: hematology at least monthly, renal function and liver function every 1 to 2 months. More frequent monitoring is usually indicated during antineoplastic therapy. During initial or changing doses, or during periods of increased risk of elevated methotrexate blood levels (e.g., dehydration), more frequent monitoring may also be indicated.

Transient liver function test abnormalities are observed frequently after methotrexate administration and are usually not cause for modification of methotrexate therapy. Persistent liver function test abnormalities, and/or depression of serum albumin may be indicators of serious liver toxicity and require evaluation. (See PRECAUTIONS, Organ System Toxicity, Hepatic).

A relationship between abnormal liver function tests and fibrosis or cirrhosis of the liver has not been established for patients with psoriasis. Persistent abnormalities in liver function tests may precede appearance of fibrosis or cirrhosis in the rheumatoid arthritis population.

Pulmonary function tests may be useful if methotrexate-induced lung disease is suspected, especially if baseline measurements are available.

Drug Interactions

Nonsteroidal anti-inflammatory drugs should not be administered prior to or concomitantly with the high doses of methotrexate, such as used in the treatment of osteosarcoma. Concomitant administration of some NSAIDs with high-dose methotrexate therapy has been reported to elevate and prolong serum methotrexate levels, resulting in deaths from severe hematologic and gastrointestinal toxicity.

Caution should be used when NSAIDs and salicylates are administered concomitantly with lower doses of methotrexate. These drugs have been reported to reduce the tubular secretion of methotrexate in an animal model and may enhance its toxicity.

Despite the potential interactions, studies of methotrexate in patients with rheumatoid arthritis have usually included concurrent use of constant dosage regimens of NSAIDs, without apparent problems. It should be appreciated, however, that the doses used in rheumatoid arthritis (7.5 to 15 mg/week) are somewhat lower than those used in psoriasis and that larger doses could lead to unexpected toxicity.

Methotrexate is partially bound to serum albumin, and toxicity may be increased because of displacement by certain drugs, such as salicylates, phenylbutazone, phenytoin, and sulfonamides. Renal tubular transport is also diminished by probenecid; use of methotrexate with this drug should be carefully monitored.

In the treatment of patients with osteosarcoma, caution must be exercised if high-dose methotrexate is administered in combination with a potentially nephrotoxic chemotherapeutic agent (e.g., cisplatin).

Methotrexate increases the plasma levels of mercaptopurine. The combination of methotrexate and mercaptopurine may therefore require dose adjustment.

Oral antibiotics such as tetracycline, chloramphenicol, and nonabsorbable broad spectrum antibiotics, may decrease intestinal absorption of methotrexate or interfere with the enterohepatic circulation by inhibiting bowel flora and suppressing metabolism of the drug by bacteria.

Penicillins may reduce the renal clearance of methotrexate; increased serum concentrations of methotrexate with concomitant hematologic and gastrointestinal toxicity have been observed with high and low dose methotrexate. Use of methotrexate with penicillins should be carefully monitored.

The potential for increased hepatotoxicity when methotrexate is administered with other hepatotoxic agents has not been evaluated. However, hepatotoxicity has been reported in such cases. Therefore, patients receiving concomitant therapy with methotrexate and other potential hepatotoxins (e.g., azathioprine, retinoids, sulfasalazine) should be closely monitored for possible increased risk of hepatotoxicity.

Methotrexate may decrease the clearance of theophylline; theophylline levels should be monitored when used concurrently with methotrexate.

Vitamin preparations containing folic acid or its derivatives may decrease responses to systemically administered methotrexate. Preliminary animal and human studies have shown that small quantities of intravenously administered leucovorin enter the CSF primarily as 5-methyltetrahydrofolate and, in humans, remain 1 to 3 orders of magnitude lower than the usual methotrexate concentrations following intrathecal administration. However, high doses of leucovorin may reduce the efficacy of intrathecally administered methotrexate.

Folate deficiency states may increase methotrexate toxicity. Trimethoprim/sulfamethoxazole has been reported rarely to increase bone marrow suppression in patients receiving methotrexate, probably by decreased tubular secretion and/or an additive antifolate effect.

The use of nitrous oxide anesthesia potentiates the effect of methotrexate on folate-dependent metabolic pathways, resulting in the potential for increased toxicity such as stomatitis, myelosuppression, and neurotoxicity. Avoid concomitant nitrous oxide anesthesia in patients receiving methotrexate. Use caution when administering methotrexate after a recent history of nitrous oxide administration.

Carcinogenesis, Mutagenesis, Impairment of Fertility

No controlled human data exist regarding the risk of neoplasia with methotrexate. Methotrexate has been evaluated in a number of animal studies for carcinogenic potential with inconclusive results. Although there is evidence that methotrexate causes chromosomal damage to animal somatic cells and human bone marrow cells, the clinical significance remains uncertain. Non-Hodgkin's lymphoma and other tumors have been reported in patients receiving low-dose oral methotrexate. However, there have been instances of malignant lymphoma arising during treatment with low-dose oral methotrexate, which have regressed completely following withdrawal of methotrexate, without requiring active anti-lymphoma treatment. Benefits should be weighed against the potential risk before using methotrexate alone or in combination with other drugs, especially in pediatric patients or young adults. Methotrexate causes embryotoxicity, abortion, and fetal defects in humans. It has also been reported to cause impairment of fertility, oligospermia and menstrual dysfunction in humans, during and for a short period after cessation of therapy.

Pregnancy

Teratogenic Effects, Pregnancy Category X

Psoriasis and rheumatoid arthritis: Methotrexate is in Pregnancy Category X (See CONTRAINDICATIONS).

Nursing Mothers

See CONTRAINDICATIONS.

Pediatric Use

Safety and effectiveness in pediatric patients have been established only in cancer chemotherapy and in polyarticular-course juvenile rheumatoid arthritis.

Published clinical studies evaluating the use of methotrexate in children and adolescents (i.e., patients 2 to 16 years of age) with JRA demonstrated safety comparable to that observed in adults with rheumatoid arthritis (see CLINICAL PHARMACOLOGY, ADVERSE REACTIONS and DOSAGE AND ADMINISTRATION.)

For intrathecal and high-dose methotrexate therapy, use the preservative-free formulation of methotrexate. Do not use the preserved formulation of methotrexate for intrathecal or high-dose therapy because it contains benzyl alcohol.

Use the preservative-free formulation of methotrexate in neonates. There have been reports of fatal “gasping syndrome” in neonates (children less than one month of age) following the administration of intravenous solutions containing the preservative benzyl alcohol. Symptoms include a striking onset of gasping respiration, hypotension, bradycardia, and cardiovascular collapse.

Serious neurotoxicity, frequently manifested as generalized or focal seizures, has been reported with unexpectedly increased frequency among pediatric patients with acute lymphoblastic leukemia who were treated with intermediate-dose intravenous methotrexate (1 gm/m^2). (See PRECAUTIONS, Organ System Toxicity, Neurologic).

Geriatric Use

Clinical studies of methotrexate did not include sufficient numbers of subjects age 65 and over to determine whether they respond differently from younger subjects. In general, dose selection for an elderly patient should be cautious reflecting the greater frequency of decreased hepatic and renal function, decreased folate stores, concomitant disease or other drug therapy (i.e., that interfere with renal function, methotrexate or folate metabolism) in this population (See PRECAUTIONS, Drug Interactions). Since decline in renal function may be associated with increases in adverse events and serum creatinine measurements may over estimate renal function in the elderly, more accurate methods (i.e., creatinine clearance) should be considered. Serum methotrexate levels may also be helpful. Elderly patients should be closely monitored for early signs of hepatic, bone marrow and renal toxicity. In chronic use situations, certain toxicities may be reduced by folate supplementation. Post- marketing experience suggests that the occurrence of bone marrow suppression, thrombocytopenia, and pneumonitis may increase with age. See Boxed WARNINGSand ADVERSE REACTIONS.

Organ System Toxicity

Gastrointestinal

If vomiting, diarrhea, or stomatitis occur, which may result in dehydration, methotrexate should be discontinued until recovery occurs. Methotrexate should be used with extreme caution in the presence of peptic ulcer disease or ulcerative colitis.

Hematologic

Methotrexate can suppress hematopoiesis and cause anemia, aplastic anemia, pancytopenia, leukopenia, neutropenia, and/or thrombocytopenia. In patients with malignancy and preexisting hematopoietic impairment, the drug should be used with caution, if at all. In controlled clinical trials in rheumatoid arthritis (n=128), leukopenia (WBC <3000/mm^3) was seen in 2 patients, thrombocytopenia (platelets <100,000/mm^3) in 6 patients, and pancytopenia in 2 patients.

In psoriasis and rheumatoid arthritis, methotrexate should be stopped immediately if there is a significant drop in blood counts. In the treatment of neoplastic diseases, methotrexate should be continued only if the potential benefit warrants the risk of severe myelosuppression. Patients with profound granulocytopenia and fever should be evaluated immediately and usually require parenteral broad-spectrum antibiotic therapy.

Hepatic

Methotrexate has the potential for acute (elevated transaminases) and chronic (fibrosis and cirrhosis) hepatotoxicity. Chronic toxicity is potentially fatal; it generally has occurred after prolonged use (generally two years or more) and after a total dose of at least 1.5 grams. In studies in psoriatic patients, hepatotoxicity appeared to be a function of total cumulative dose and appeared to be enhanced by alcoholism, obesity, diabetes, and advanced age. An accurate incidence rate has not been determined; the rate of progression and reversibility of lesions is not known. Special caution is indicated in the presence of preexisting liver damage or impaired hepatic function.

In psoriasis, liver function tests, including serum albumin, should be performed periodically prior to dosing but are often normal in the face of developing fibrosis or cirrhosis. These lesions may be detectable only by biopsy. The usual recommendation is to obtain a liver biopsy at 1) pretherapy or shortly after initiation of therapy (2 to 4 months), 2) a total cumulative dose of 1.5 grams, and 3) after each additional 1 to 1.5 grams. Moderate fibrosis or any cirrhosis normally leads to discontinuation of the drug; mild fibrosis normally suggests a repeat biopsy in 6 months. Milder histologic findings such as fatty change and low grade portal inflammation, are relatively common pretherapy. Although these mild changes are usually not a reason to avoid or discontinue methotrexate therapy, the drug should be used with caution.

In rheumatoid arthritis, age at first use of methotrexate and duration of therapy have been reported as risk factors for hepatotoxicity; other risk factors, similar to those observed in psoriasis, may be present in rheumatoid arthritis but have not been confirmed to date. Persistent abnormalities in liver function tests may precede appearance of fibrosis or cirrhosis in this population. There is a combined reported experience in 217 rheumatoid arthritis patients with liver biopsies both before and during treatment (after a cumulative dose of at least 1.5 g) and in 714 patients with a biopsy only during treatment. There are 64 (7%) cases of fibrosis and 1 (0.1%) case of cirrhosis. Of the 64 cases of fibrosis, 60 were deemed mild. The reticulin stain is more sensitive for early fibrosis and its use may increase these figures. It is unknown whether even longer use will increase these risks.

Liver function tests should be performed at baseline and at 4 to 8 week intervals in patients receiving methotrexate for rheumatoid arthritis. Pretreatment liver biopsy should be performed for patients with a history of excessive alcohol consumption, persistently abnormal baseline liver function test values or chronic hepatitis B or C infection. During therapy, liver biopsy should be performed if there are persistent liver function test abnormalities or there is a decrease in serum albumin below the normal range (in the setting of well controlled rheumatoid arthritis).

If the results of a liver biopsy show mild changes (Roenigk, grades I, II, IIIa), methotrexate may be continued and the patient monitored as per recommendations listed above. Methotrexate should be discontinued in any patient who displays persistently abnormal liver function tests and refuses liver biopsy or in any patient whose liver biopsy shows moderate to severe changes (Roenigk grade IIIb or IV).

Infection or Immunologic States

Methotrexate should be used with extreme caution in the presence of active infection, and is usually contraindicated in patients with overt or laboratory evidence of immunodeficiency syndromes. Immunization may be ineffective when given during methotrexate therapy. Immunization with live virus vaccines is generally not recommended. There have been reports of disseminated vaccinia infections after smallpox immunizations in patients receiving methotrexate therapy. Hypogammaglobulinemia has been reported rarely.

Potentially fatal opportunistic infections, especially Pneumocystis carinii pneumonia, may occur with methotrexate therapy. When a patient presents with pulmonary symptoms, the possibility of Pneumocystis carinii pneumonia should be considered.

Neurologic

There have been reports of leukoencephalopathy following intravenous administration of methotrexate to patients who have had craniospinal irradiation. Serious neurotoxicity, frequently manifested as generalized or focal seizures, has been reported with unexpectedly increased frequency among pediatric patients with acute lymphoblastic leukemia who were treated with intermediate-dose intravenous methotrexate (1 gm/m^2). Symptomatic patients were commonly noted to have leukoencephalopathy and/or microangiopathic calcifications on diagnostic imaging studies. Chronic leukoencephalopathy has also been reported in patients who received repeated doses of high-dose methotrexate with leucovorin rescue even without cranial irradiation. Discontinuation of methotrexate does not always result in complete recovery.

A transient acute neurologic syndrome has been observed in patients treated with high-dose regimens. Manifestations of this stroke-like encephalopathy may include confusion, hemiparesis, transient blindness, seizures and coma. The exact cause is unknown.

After the intrathecal use of methotrexate, the central nervous system toxicity which may occur can be classified as follows: acute chemical arachnoiditis manifested by such symptoms as headache, back pain, nuchal rigidity, and fever; sub-acute myelopathy characterized by paraparesis/paraplegia associated with involvement with one or more spinal nerve roots; chronic leukoencephalopathy manifested by confusion, irritability, somnolence, ataxia, dementia, seizures and coma. This condition can be progressive and even fatal.

Pulmonary

Pulmonary symptoms (especially a dry nonproductive cough) or a non-specific pneumonitis occurring during methotrexate therapy may be indicative of a potentially dangerous lesion and require interruption of treatment and careful investigation. Although clinically variable, the typical patient with methotrexate induced lung disease presents with fever, cough, dyspnea, hypoxemia, and an infiltrate on chest X-ray; infection (including pneumonia) needs to be excluded. This lesion can occur at all dosages.

Renal

Methotrexate may cause renal damage that may lead to acute renal failure. High doses of methotrexate used in the treatment of osteosarcoma may cause renal damage leading to acute renal failure. Nephrotoxicity is due primarily to the precipitation of methotrexate and 7-hydroxymethotrexate in the renal tubules. Close attention to renal function including adequate hydration, urine alkalinization and measurement of serum methotrexate and creatinine levels are essential for safe administration.

Skin

Severe, occasionally fatal, dermatologic reactions, including toxic epidermal necrolysis, Stevens-Johnson syndrome, exfoliative dermatitis, skin necrosis, and erythema multiforme, have been reported in children and adults, within days of oral, intramuscular, intravenous, or intrathecal methotrexate administration. Reactions were noted after single or multiple low, intermediate, or high doses of methotrexate in patients with neoplastic and non-neoplastic diseases.

Other Precautions

Methotrexate should be used with extreme caution in the presence of debility.

Methotrexate exits slowly from third space compartments (e.g., pleural effusions or ascites). This results in a prolonged terminal plasma half-life and unexpected toxicity. In patients with significant third space accumulations, it is advisable to evacuate the fluid before treatment and to monitor plasma methotrexate levels.

Lesions of psoriasis may be aggravated by concomitant exposure to ultraviolet radiation. Radiation dermatitis and sunburn may be “recalled” by the use of methotrexate.

ADVERSE REACTIONS

IN GENERAL, THE INCIDENCE AND SEVERITY OF ACUTE SIDE EFFECTS ARE RELATED TO DOSE AND FREQUENCY OF ADMINISTRATION. THE MOST SERIOUS REACTIONS ARE DISCUSSED ABOVE UNDER ORGAN SYSTEM TOXICITY IN THE PRECAUTIONS SECTION. THAT SECTION SHOULD ALSO BE CONSULTED WHEN LOOKING FOR INFORMATION ABOUT ADVERSE REACTIONS WITH METHOTREXATE.

The most frequently reported adverse reactions include ulcerative stomatitis, leukopenia, nausea, and abdominal distress. Other frequently reported adverse effects are malaise, undue fatigue, chills and fever, dizziness and decreased resistance to infection.

Other adverse reactions that have been reported with methotrexate are listed below by organ system. In the oncology setting, concomitant treatment and the underlying disease make specific attribution of a reaction to methotrexate difficult.

Alimentary System - gingivitis, pharyngitis, stomatitis, anorexia, nausea, vomiting, diarrhea, hematemesis, melena, gastrointestinal ulceration and bleeding, enteritis, pancreatitis.

Blood and Lymphatic System Disorders - suppressed hematopoiesis, anemia, aplastic anemia, pancytopenia, leukopenia, neutropenia, thrombocytopenia, agranulocytosis, eosinophilia, lymphadenopathy and lymphoproliferative disorders (including reversible). Hypogammaglobulinemia has been reported rarely.

Cardiovascular - pericarditis, pericardial effusion, hypotension, and thromboembolic events (including arterial thrombosis, cerebral thrombosis, deep vein thrombosis, retinal vein thrombosis, thrombophlebitis, and pulmonary embolus).

Central Nervous System - headaches, drowsiness, blurred vision, transient blindness, speech impairment including dysarthria and aphasia, hemiparesis, paresis and convulsions have also occurred following administration of methotrexate. Following low doses, there have been occasional reports of transient subtle cognitive dysfunction, mood alteration, or unusual cranial sensations, leukoencephalopathy, or encephalopathy.

Hepatobiliary Disorders - hepatotoxicity, acute hepatitis, chronic fibrosis and cirrhosis, hepatic failure, decrease in serum albumin, liver enzyme elevations.

Infection - There have been case reports of sometimes fatal opportunistic infections in patients receiving methotrexate therapy for neoplastic and non-neoplastic diseases. Pneumocystis carinii pneumonia was the most common opportunistic infection. There have also been reports of infections, pneumonia, Cytomegalovirus infection, including cytomegaloviral pneumonia, sepsis, fatal sepsis, nocardiosis; histoplasmosis, cryptococcosis, Herpes zoster, H. simplex hepatitis, and disseminated

H. simplex.

Musculoskeletal System - stress fracture.

Ophthalmic - conjunctivitis, serious visual changes of unknown etiology.

Pulmonary System – respiratory fibrosis, respiratory failure, alveolitis, interstitial pneumonitis deaths have been reported, and chronic interstitial obstructive pulmonary disease has occasionally occurred.

Skin - erythematous rashes, pruritus, urticaria, photosensitivity, pigmentary changes, alopecia, ecchymosis, telangiectasia, acne, furunculosis, erythema multiforme, toxic epidermal necrolysis, Stevens-Johnson syndrome, skin necrosis, skin ulceration, and exfoliative dermatitis.

Urogenital System - severe nephropathy or renal failure, azotemia, cystitis, hematuria, proteinuria; defective oogenesis or spermatogenesis, transient oligospermia, menstrual dysfunction, vaginal discharge, and gynecomastia; infertility, abortion, fetal death, fetal defects.

Other rarer reactions related to or attributed to the use of methotrexate such as nodulosis, vasculitis, arthralgia/myalgia, loss of libido/impotence, diabetes, osteoporosis, sudden death, lymphoma, including reversible lymphomas, tumor lysis syndrome, soft tissue necrosis, and osteonecrosis. Anaphylactoid reactions have been reported.

Adverse Reactions in Double-Blind Rheumatoid Arthritis Studies

The approximate incidences of methotrexate-attributed (i.e., placebo rate subtracted) adverse reactions in 12 to 18 week double-blind studies of patients (n=128) with rheumatoid arthritis treated with low-dose oral (7.5 to 15 mg/week) pulse methotrexate, are listed below. Virtually all of these patients were on concomitant nonsteroidal anti-inflammatory drugs and some were also taking low dosages of corticosteroids. Hepatic histology was not examined in these short-term studies. (See PRECAUTIONS).

Incidence greater than 10%: Elevated liver function tests 15%, nausea/vomiting 10%.

Incidence 3% to 10%: Stomatitis, thrombocytopenia (platelet count less than 100,000/mm^3).

Incidence 1% to 3%: Rash/pruritus/dermatitis, diarrhea, alopecia, leukopenia (WBC less than 3000/mm^3), pancytopenia, dizziness.

Two other controlled trials of patients (n=680) with Rheumatoid Arthritis on 7.5 mg to 15 mg/wk oral doses showed an incidence of interstitial pneumonitis of 1%. (See PRECAUTIONS.)

Other less common reactions included decreased hematocrit, headache, upper respiratory infection, anorexia, arthralgias, chest pain, coughing, dysuria, eye discomfort, epistaxis, fever, infection, sweating, tinnitus, and vaginal discharge.

Adverse Reactions in Psoriasis

There are no recent placebo-controlled trials in patients with psoriasis. There are two literature reports (Roenigk, 1969, and Nyfors, 1978) describing large series (n=204, 248) of psoriasis patients treated with methotrexate. Dosages ranged up to 25 mg per week and treatment was administered for up to four years. With the exception of alopecia, photosensitivity, and “burning of skin lesions” (each 3% to 10%), the adverse reaction rates in these reports were very similar to those in the rheumatoid arthritis studies. Rarely, painful plaque erosions may appear (Pearce, HP and Wilson, BB: Am Acad Dermatol 35: 835-838, 1996).

Adverse Reactions in JRA Studies

The approximate incidences of adverse reactions reported in pediatric patients with JRA treated with oral, weekly doses of methotrexate (5 to 20 mg/m^2/wk or 0.1 to0.65 mg/kg/wk) were as follows (virtually all patients were receiving concomitant nonsteroidal anti-inflammatory drugs, and some also were taking low doses of corticosteroids): elevated liver function tests, 14%; gastrointestinal reactions (e.g., nausea, vomiting, diarrhea), 11%; stomatitis, 2%; leukopenia, 2%; headache, 1.2%; alopecia, 0.5%; dizziness, 0.2%; and rash, 0.2%. Although there is experience with dosing up to 30 mg/m^2/wk in JRA, the published data for doses above 20 mg/m^2/wk are too limited to provide reliable estimates of adverse reaction rates.

OVERDOSAGE

Leucovorin is indicated to diminish the toxicity and counteract the effect of inadvertently administered overdosages of methotrexate. Leucovorin administration should begin as promptly as possible. As the time interval between methotrexate administration and leucovorin initiation increases, the effectiveness of leucovorin in counteracting toxicity decreases. Monitoring of the serum methotrexate concentration is essential in determining the optimal dose and duration of treatment with leucovorin.

In cases of massive overdosage, hydration and urinary alkalinization may be necessary to prevent the precipitation of methotrexate and/or its metabolites in the renal tubules. Generally speaking, neither hemodialysis nor peritoneal dialysis has been shown to improve methotrexate elimination. However, effective clearance of methotrexate has been reported with acute, intermittent hemodialysis using a high-flux dialyzer (Wall, SM et al: Am J Kidney Dis 28(6): 846-854, 1996).

Accidental intrathecal overdosage may require intensive systemic support, high-dose systemic leucovorin, alkaline diuresis and rapid CSF drainage and ventriculolumbar perfusion.

In postmarketing experience, overdose with methotrexate has generally occurred with oral and intrathecal administration, although intravenous and intramuscular overdose have also been reported.

Reports of oral overdose often indicate accidental daily administration instead of weekly (single or divided doses). Symptoms commonly reported following oral overdose include those symptoms and signs reported at pharmacologic doses, particularly hematologic and gastrointestinal reaction. For example, leukopenia, thrombocytopenia, anemia, pancytopenia, bone marrow suppression, mucositis, stomatitis, oral ulceration, nausea, vomiting, gastrointestinal ulceration, gastrointestinal bleeding. In some cases, no symptoms were reported. There have been reports of death following overdose. In these cases, events such as sepsis or septic shock, renal failure, and aplastic anemia were also reported.

Symptoms of intrathecal overdose are generally central nervous system (CNS) symptoms, including headache, nausea and vomiting, seizure or convulsion, and acute toxic encephalopathy. In some cases, no symptoms were reported. There have been reports of death following intrathecal overdose. In these cases, cerebellar herniation associated with increased intracranial pressure, and acute toxic encephalopathy have also been reported.

Glucarpidase is indicated for the treatment of toxic methotrexate concentrations in patients with delayed methotrexate clearance due to impaired renal function (refer to the glucarpidase prescribing information).

If glucarpidase is used, do not administer leucovorin within two hours before or after a dose of glucarpidase because leucovorin is a substrate for glucarpidase. There are published case reports of intravenous and intrathecal glucarpidase treatment to hasten clearance of methotrexate in cases of overdose.

DOSAGE AND ADMINISTRATION

Neoplastic Diseases

For intrathecal and high-dose methotrexate therapy, use the preservative-free formulation of methotrexate. Do not use the preserved formulation of methotrexate for intrathecal or high-dose therapy because it contains benzyl alcohol.

Oral administration in tablet form is often preferred when low doses are being administered since absorption is rapid and effective serum levels are obtained. Methotrexate sodium (preservative free) injectable products may be given by the intramuscular, intravenous, intra-arterial or intrathecal route.

Choriocarcinoma and similar trophoblastic diseases- Methotrexate is administered orally or intramuscularly in doses of 15 to 30 mg daily for a five-day course. Such courses are usually repeated for 3 to 5 times as required, with rest periods of one or more weeks interposed between courses, until any manifesting toxic symptoms subside. The effectiveness of therapy is ordinarily evaluated by 24 hour quantitative analysis of urinary chorionic gonadotropin (hCG), which should return to normal or less than 50 IU/24 hr usually after the third or fourth course and usually be followed by a complete resolution of measurable lesions in 4 to 6 weeks. One to two courses of methotrexate after normalization of hCG is usually recommended. Before each course of the drug careful clinical assessment is essential. Cyclic combination therapy of methotrexate with other antitumor drugs has been reported as being useful.

Since hydatidiform mole may precede choriocarcinoma, prophylactic chemotherapy with methotrexate has been recommended.

Chorioadenoma destruens is considered to be an invasive form of hydatidiform mole.

Methotrexate is administered in these disease states in doses similar to those recommended for choriocarcinoma.

Leukemia- Acute lymphoblastic leukemia in pediatric patients and young adolescents is the most responsive to present day chemotherapy. In young adults and older patients, clinical remission is more difficult to obtain and early relapse is more common.

Methotrexate alone or in combination with steroids was used initially for induction of remission in acute lymphoblastic leukemias. More recently corticosteroid therapy, in combination with other antileukemic drugs or in cyclic combinations with methotrexate included, has appeared to produce rapid and effective remissions. When used for induction, methotrexate in doses of 3.3 mg/m^2 in combination with 60 mg/m^2 of prednisone, given daily, produced remissions in 50% of patients treated, usually within a period of 4 to 6 weeks. Methotrexate in combination with other agents appears to be the drug of choice for securing maintenance of drug-induced remissions. When remission is achieved and supportive care has produced general clinical improvement, maintenance therapy is initiated, as follows: Methotrexate is administered 2 times weekly either by mouth or intramuscularly in total weekly doses of 30 mg/m^2. It has also been given in doses of 2.5 mg/kg intravenously every 14 days. If and when relapse does occur, reinduction of remission can again usually be obtained by repeating the initial induction regimen.

A variety of combination chemotherapy regimens have been used for both induction and maintenance therapy in acute lymphoblastic leukemia. The physician should be familiar with the new advances in antileukemic therapy.

Meningeal Leukemia- In the treatment of prophylaxis of meningeal leukemia, methotrexate must be administered intrathecally. Dilute preservative free methotrexate to a concentration of 1 mg/mL in an appropriate sterile, preservative free medium such as 0.9% Sodium Chloride Injection, USP.

The cerebrospinal fluid volume is dependent on age and not body surface area. The CSF is at 40% of the adult volume at birth and reaches the adult volume in several years.

Intrathecal methotrexate administration at a dose of 12 mg/m^2 (maximum 15 mg) has been reported to result in low CSF methotrexate concentrations and reduced efficacy in pediatric patients and high concentrations and neurotoxicity in adults. The following dosage regimen is based on age instead of body surface area:

Age (years) | Dose (mg)
<1 | 6
1 | 8
2 | 10
3 or older | 12

In one study in patients under the age of 40, this dosage regimen appeared to result in more consistent CSF methotrexate concentrations and less neurotoxicity. Another study in pediatric patients with acute lymphocytic leukemia compared this regimen to a dose of 12 mg/m^2 (maximum 15 mg), a significant reduction in the rate of CNS relapse was observed in the group whose dose was based on age.

Because the CSF volume and turnover may decrease with age, a dose reduction may be indicated in elderly patients.

For the treatment of meningeal leukemia, intrathecal methotrexate may be given at intervals of 2 to 5 days. However, administration at intervals of less than 1 week may result in increased subacute toxicity. Methotrexate is administered until the cell count of the cerebrospinal fluid returns to normal. At this point one additional dose is advisable.

For prophylaxis against meningeal leukemia, the dosage is the same as for treatment except for the intervals of administration. On this subject, it is advisable for the physician to consult the medical literature.

Untoward side effects may occur with any given intrathecal injection and are commonly neurological in character. Large doses may cause convulsions. Methotrexate given by the intrathecal route appears significantly in the systemic circulation and may cause systemic methotrexate toxicity. Therefore, systemic antileukemic therapy with the drug should be appropriately adjusted, reduced or discontinued. Focal leukemic involvement of the central nervous system may not respond to intrathecal chemotherapy and is best treated with radiotherapy.

Lymphomas- In Burkitt’s tumor, Stages I-II, methotrexate has produced prolonged remissions in some cases. Recommended dosage is 10 to 25 mg/day orally for 4 to 8 days. In Stage III, methotrexate is commonly given concomitantly with other antitumor agents. Treatment in all stages usually consists of several courses of the drug interposed with 7 to 10 day rest periods. Lymphosarcomas in Stage III may respond to combined drug therapy with methotrexate given in doses of 0.625 to 2.5 mg/kg daily.

Mycosis fungoides (cutaneous T cell lymphoma) - Therapy with methotrexate as a single agent appears to produce clinical responses in up to 50% of patients treated. Dosage in early stages is usually 5 to 50 mg once weekly. Dose reduction or cessation is guided by patient response and hematologic monitoring. Methotrexate has also been administered twice weekly in doses ranging from 15 to 37.5 mg in patients who have responded poorly to weekly therapy. Combination chemotherapy regimens that include intravenous methotrexate administered at higher doses with leucovorin rescue have been utilized in advanced stages of the disease.

Osteosarcoma- An effective adjuvant chemotherapy regimen requires the administration of several cytotoxic chemotherapeutic agents. In addition to high-dose methotrexate with leucovorin rescue, these agents may include doxorubicin, cisplatin, and the combination of bleomycin, cyclophosphamide and dactinomycin (BCD) in the doses and schedule shown in the table below. The starting dose for high-dose methotrexate treatment is 12 grams/m^2. If this dose is not sufficient to produce a peak serum methotrexate concentration of 1,000 micromolar (10^-3 mol/L) at the end of the methotrexate infusion, the dose may be escalated to 15 grams/m^2 in subsequent treatments. If the patient is vomiting or is unable to tolerate oral medication, leucovorin is given IV or IM at the same dose and schedule.

Drug* | Dose* | Treatment Week After Surgery
Methotrexate | 12 g/m^2 IV as 4 hour infusion (starting dose) | 4,5,6,7,11,12,15,16,29,30,44,45
Leucovorin | 15 mg orally every six hours for 10 doses starting at 24 hours after start of methotrexate infusion. | ---------
Doxorubicin† as a single drug | 30 mg/m^2/day IV x 3 days | 8,17
Doxorubicin† | 50 mg/m^2 IV | 20,23,33,36
Cisplatin† | 100 mg/m^2 IV | 20,23,33,36
Bleomycin† | 15 units/m^2 IV x 2 days | 2,13,26,39,42
Cyclophosphamide† | 600 mg/m^2 IV x 2 days | 2,13,26,39,42
Dactinomycin† | 0.6 mg/m^2 IV x 2 days | 2,13,26,39,42

* Link MP, Goorin AM, Miser AW, et al: The effect of adjuvant chemotherapy on relapse-free survival in patients with osteosarcoma of the extremity. N Engl J of Med 1986; 314(No.25): 1600-1606.

† See each respective package insert for full prescribing information. Dosage modifications may be necessary because of drug-induced toxicity.

When these higher doses of methotrexate are to be administered, the following safety guidelines should be closely observed.

GUIDELINES FOR METHOTREXATE THERAPY WITH LEUCOVORIN RESCUE

1. Administration of methotrexate should be delayed until recovery if:
  - the WBC count is less than 1500/microliter
  - the neutrophil count is less than 200/microliter
  - the platelet count is less than 75,000/microliter
  - the serum bilirubin level is greater than 1.2 mg/dL
  - the SGPT level is greater than 450 U
  - mucositis is present, until there is evidence of healing
  - persistent pleural effusion is present; this should be drained dry prior to infusion.
2. Adequate renal function must be documented.
  1. Serum creatinine must be normal, and creatinine clearance must be greater than 60 mL/min, before initiation of therapy.
  2. Serum creatinine must be measured prior to each subsequent course of therapy. If serum creatinine has increased by 50% or more compared to a prior value, the creatinine clearance must be measured and documented to be greater than 60 mL/min (even if the serum creatinine is still within the normal range).
3. Patients must be well hydrated, and must be treated with sodium bicarbonate for urinary alkalinization.
  1. Administer 1,000 mL/m^2 of intravenous fluid over 6 hours prior to initiation of the methotrexate infusion. Continue hydration at 125 mL/m^2/hr (3 liters/m^2/day) during the methotrexate infusion, and for 2 days after the infusion has been completed.
  2. Alkalinize urine to maintain pH above 7.0 during methotrexate infusion and leucovorin calcium therapy. This can be accomplished by the administration of sodium bicarbonate orally or by incorporation into a separate intravenous solution.
4. Repeat serum creatinine and serum methotrexate 24 hours after starting methotrexate and at least once daily until the methotrexate level is below 5 x 10^-8 mol/L (0.05 micromolar).
5. The table below provides guidelines for leucovorin calcium dosage based upon serum methotrexate levels. (See table below.‡)
  Patients who experience delayed early methotrexate elimination are likely to develop nonreversible oliguric renal failure. In addition to appropriate leucovorin therapy, these patients require continuing hydration and urinary alkalinization, and close monitoring of fluid and electrolyte status, until the serum methotrexate level has fallen to below 0.05 micromolar and the renal failure has resolved. If necessary, acute, intermittent hemodialysis with a high-flux dialyzer may also be beneficial in these patients.
6. Some patients will have abnormalities in methotrexate elimination, or abnormalities in renal function following methotrexate administration, which are significant but less severe than the abnormalities described in the table below. These abnormalities may or may not be associated with significant clinical toxicity. If significant clinical toxicity is observed, leucovorin rescue should be extended for an additional 24 hours (total 14 doses over 84 hours) in subsequent courses of therapy. The possibility that the patient is taking other medications which interact with methotrexate (e.g., medications which may interfere with methotrexate binding to serum albumin, or elimination) should always be reconsidered when laboratory abnormalities or clinical toxicities are observed.

CAUTION: DO NOT ADMINISTER LEUCOVORIN INTRATHECALLY.

Psoriasis, Rheumatoid Arthritis, and Juvenile Rheumatoid Arthritis

Adult Rheumatoid Arthritis: Recommended Starting Dosage Schedules

1. Single oral doses of 7.5 mg once weekly.†
2. Divided oral dosages of 2.5 mg at 12 hour intervals for 3 doses given as a course once weekly.†

†Methotrexate Sodium Tablets for oral administration are available.

Polyarticular-Course Juvenile Rheumatoid Arthritis: The recommended starting dose is 10 mg/m^2 given once weekly.

For either adult RA or polyarticular-course JRA, dosages may be adjusted gradually to achieve an optimal response. Limited experience shows a significant increase in the incidence and severity of serious toxic reactions, especially bone marrow suppression, at doses greater than 20 mg/wk in adults. Although there is experience with doses up to 30 mg/m^2/wk in children, there are too few published data to assess how doses over 20 mg/m^2/wk might affect the risk of serious toxicity in children.

Experience does suggest, however, that children receiving 20 to 30 mg/m^2/wk (0.65 to 1 mg/kg/wk) may have better absorption and fewer gastrointestinal side effects if methotrexate is administered either intramuscularly or subcutaneously.

Therapeutic response usually begins within 3 to 6 weeks and the patient may continue to improve for another 12 weeks or more.

The optimal duration of therapy is unknown. Limited data available from long-term studies in adults indicate that the initial clinical improvement is maintained for at least two years with continued therapy. When methotrexate is discontinued, the arthritis usually worsens within 3 to 6 weeks.

The patient should be fully informed of the risks involved and should be under constant supervision of the physician. (SeeInformation for Patients underPRECAUTIONS). Assessment of hematologic, hepatic, renal, and pulmonary function should be made by history, physical examination, and laboratory tests before beginning, periodically during, and before reinstituting methotrexate therapy (See PRECAUTIONS). Appropriate steps should be taken to avoid conception during methotrexate therapy (See PRECAUTIONSand CONTRAINDICATIONS).

All schedules should be continually tailored to the individual patient. An initial test dose may be given prior to the regular dosing schedule to detect any extreme sensitivity to adverse effects (See ADVERSE REACTIONS). Maximal myelosuppression usually occurs in seven to ten days.

Psoriasis: Recommended Starting Dose Schedule

1. Weekly single oral, IM or IV dosage schedule: 10 to 25 mg per week until adequate response is achieved.†
2. Divided oral dose schedule: 2.5 mg at 12 hour intervals for three doses.†

†Methotrexate Sodium Tablets for oral administration are available.

Dosages in each schedule may be gradually adjusted to achieve optimal clinical response; 30 mg/week should not ordinarily be exceeded.

Once optimal clinical response has been achieved, each dosage schedule should be reduced to the lowest possible amount of drug and to the longest possible rest period. The use of methotrexate may permit the return to conventional topical therapy, which should be encouraged.

Handling and Disposal: Procedures for proper handling and disposal of anticancer drugs should be considered. Several guidelines on this subject have been published.^1-7 There is no general agreement that all of the procedures recommended in the guidelines are necessary or appropriate.

Reconstitution of Lyophilized Powders: Reconstitute immediately prior to use.

Methotrexate for injection should be reconstituted with an appropriate sterile, preservative free medium such as 5% dextrose solution, USP or sodium chloride injection, USP. The 1 gram vial should be reconstituted with 19.4 mL to a concentration of 50 mg/mL. When high doses of methotrexate are administered by IV infusion, the total dose is diluted in 5% dextrose solution, USP.

For intrathecal injection, reconstitute to a concentration of 1 mg/mL with an appropriate sterile, preservative free medium such as sodium chloride injection, USP.

Parenteral drug products should be inspected visually for particulate matter and discoloration prior to administration, whenever solution and container permit.

HOW SUPPLIED

Methotrexate for Injection, USP (preservative free) is supplied in a 1 gram, single-dose vial of lyophilized powder containing 1 gram methotrexate as the base in the following package strength:

NDC 0143-9367-01 1 gram Vial (individually boxed)

Store at 20° to 25°C (68° to 77°F) [See USP Controlled Room Temperature]. Protect from light.

To report SUSPECTED ADVERSE REACTIONS, contact Hikma Pharmaceuticals USA Inc. at 1-877-845-0689, or the FDA at 1-800-FDA-1088 or www.fda.gov/medwatch.

For Product Inquiry call 1-877-845-0689.

REFERENCES

-
  1. Controlling Occupational Exposure to Hazardous Drugs (OSHA Work-Practice Guidelines). Am J Health Syst Pharma 1996: 53: 1669-1685
  2. Recommendations for the Safe Handling of Parenteral Antineoplastic Drugs. NIH Publication No. 83-2621. For sale by the Superintendent of Documents, U.S. Government Printing Office, Washington, DC 20402.
  3. AMA Council Report. Guidelines for Handling Parenteral Antineoplastics. JAMA, 1985; 253(11): 1590-1592.
  4. National Study Commission on Cytotoxic Exposure-Recommendations for Handling Cytotoxic Agents. Available from Louis P. Jeffrey, ScD., Chairman, National Study Commission on Cytotoxic Exposure, Massachusetts College of Pharmacy and Allied Health Sciences, 179 Longwood Avenue, Boston, Massachusetts 02115.
  5. Clinical Oncological Society of Australia: Guidelines and Recommendations for Safe Handling of Antineoplastic Agents. Med J Australia 1983: 1: 426-428.
  6. Jones RB, et al. Safe Handling of Chemotherapeutic Agents: A Report from the Mount Sinai Medical Center. Ca-A Cancer Journal for Clinicians : Sept/Oct 1983; 258-263.
  7. American Society of Hospital Pharmacists Technical Assistance Bulletin on Handling Cytotoxic and Hazardous Drugs. Am J Hosp Pharm 1990; 47:1033- 1049.

Manufactured by

THYMOORGAN PHARMAZIE GmbH,

Schiffgraben 23, 38690 Goslar, Germany

Distributed by

Hikma Pharmaceuticals USA Inc.

Berkeley Heights 07922

Novaplus is a registered trademark of Vizient Inc.

Revised September 2020

127.207.040/01

LEUCOVORIN RESCUE SCHEDULES FOLLOWING TREATMENT WITH HIGHER DOSES OF METHOTREXATE
Clinical Situation | Laboratory Findings | Leucovorin Dosage and Duration
Normal Methotrexate Elimination | Serum methotrexate level approximately 10 micromolar at 24 hours after administration, 1 micromolar at 48 hours, and less than 0.2 micromolar at 72 hours. | 15 mg PO, IM or IV q 6 hours for 60 hours (10 doses starting at 24 hours after start of methotrexate infusion).
Delayed Late Methotrexate Elimination | Serum methotrexate level remaining above 0.2 micromolar at 72 hours, and more than 0.05 micromolar at 96 hours after administration. | Continue 15 mg PO, IM or IV q 6 hours, until methotrexate level is less than 0.05 micromolar.
Delayed Early Methotrexate Elimination and/or Evidence of Acute Renal Injury | Serum methotrexate level of 50 micromolar or more at 24 hours, or 5 micromolar or more at 48 hours after administration, OR; a 100% or greater increase in serum creatinine level at 24 hours after methotrexate administration (e.g., an increase from 0.5 mg/dL to a level of 1 mg/dL or more). | 150 mg IV q 3 hours, untilmethotrexate level is lessthan 1 micromolar; then15 mg IV q 3 hours, untilmethotrexate level is less than 0.05 micromolar.

VIAL LABEL 1 GRAM

NDC 0143-9367-01

Rx only

Methotrexate for Injection, USP

1 g/vial

Sterile, Lyophilized

Preservative-Free

Cytotoxic Agent

See package insert for routes of administration